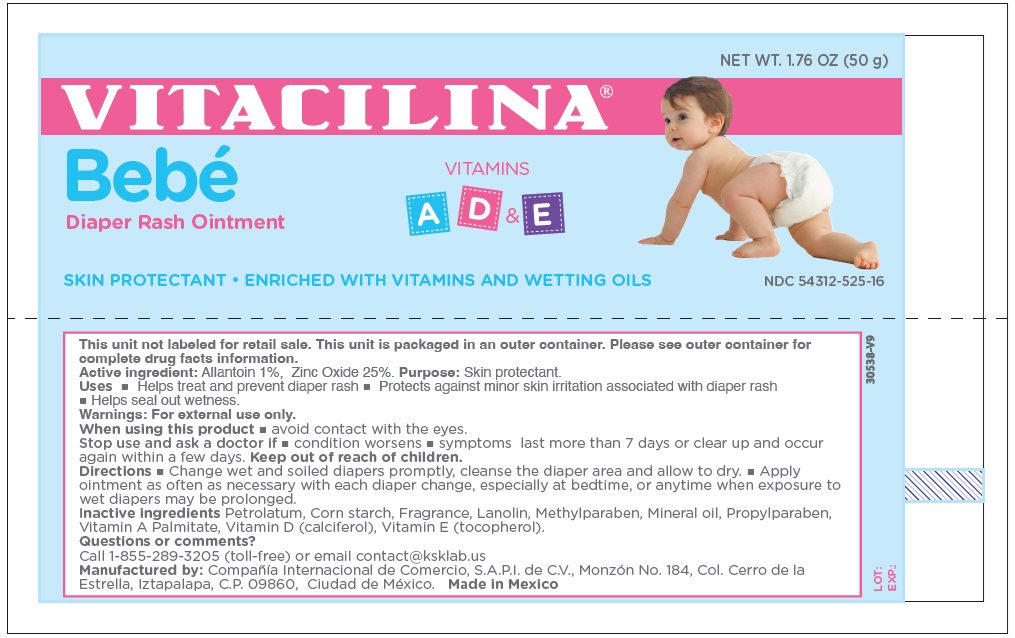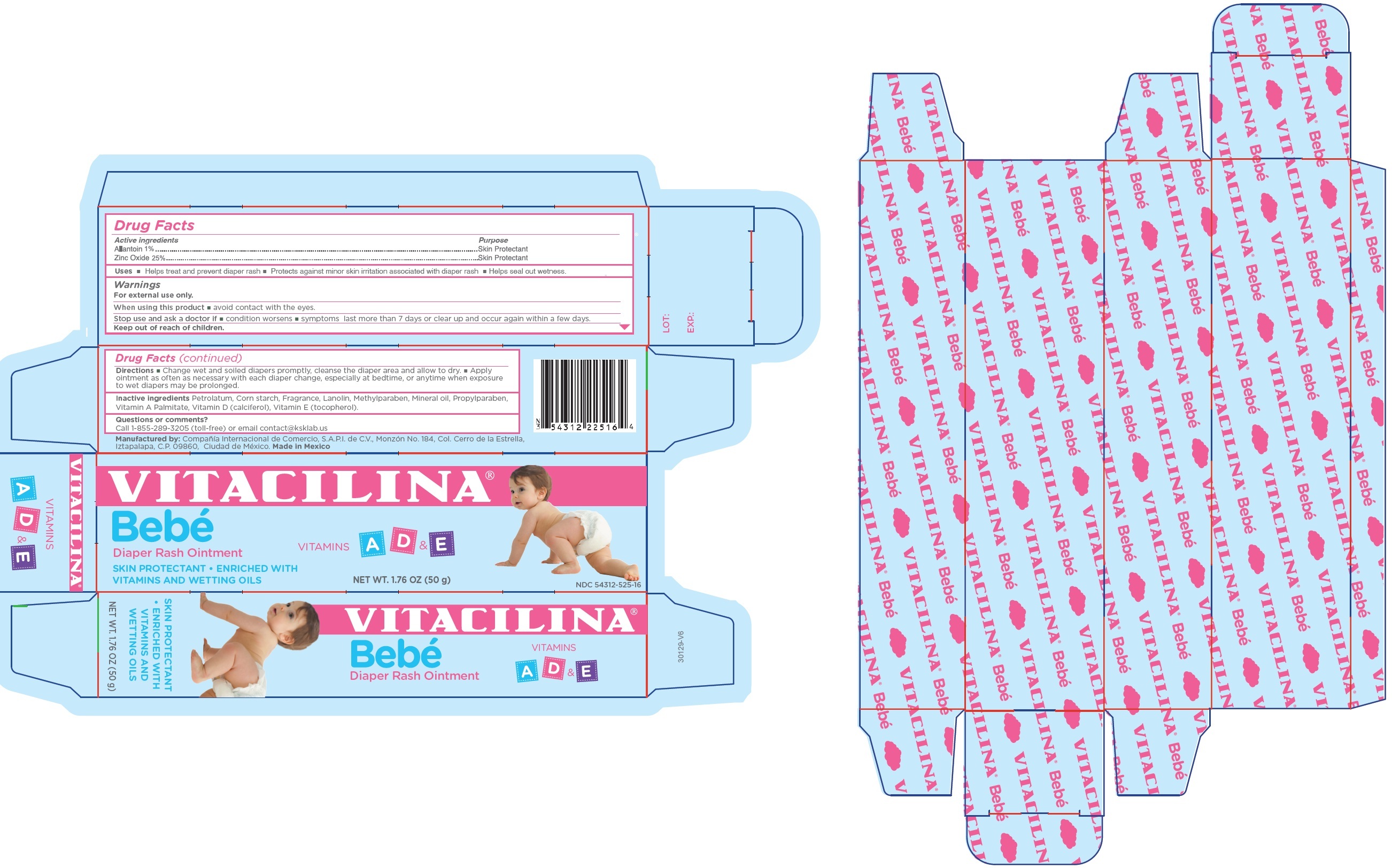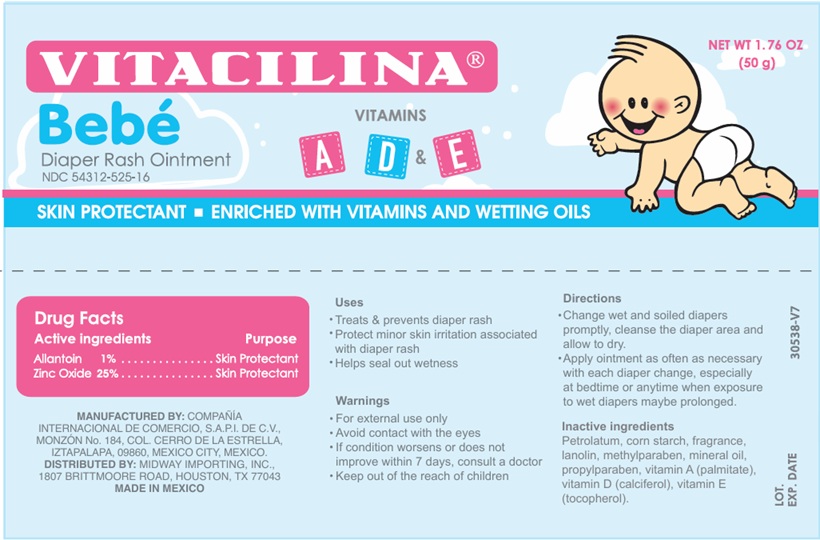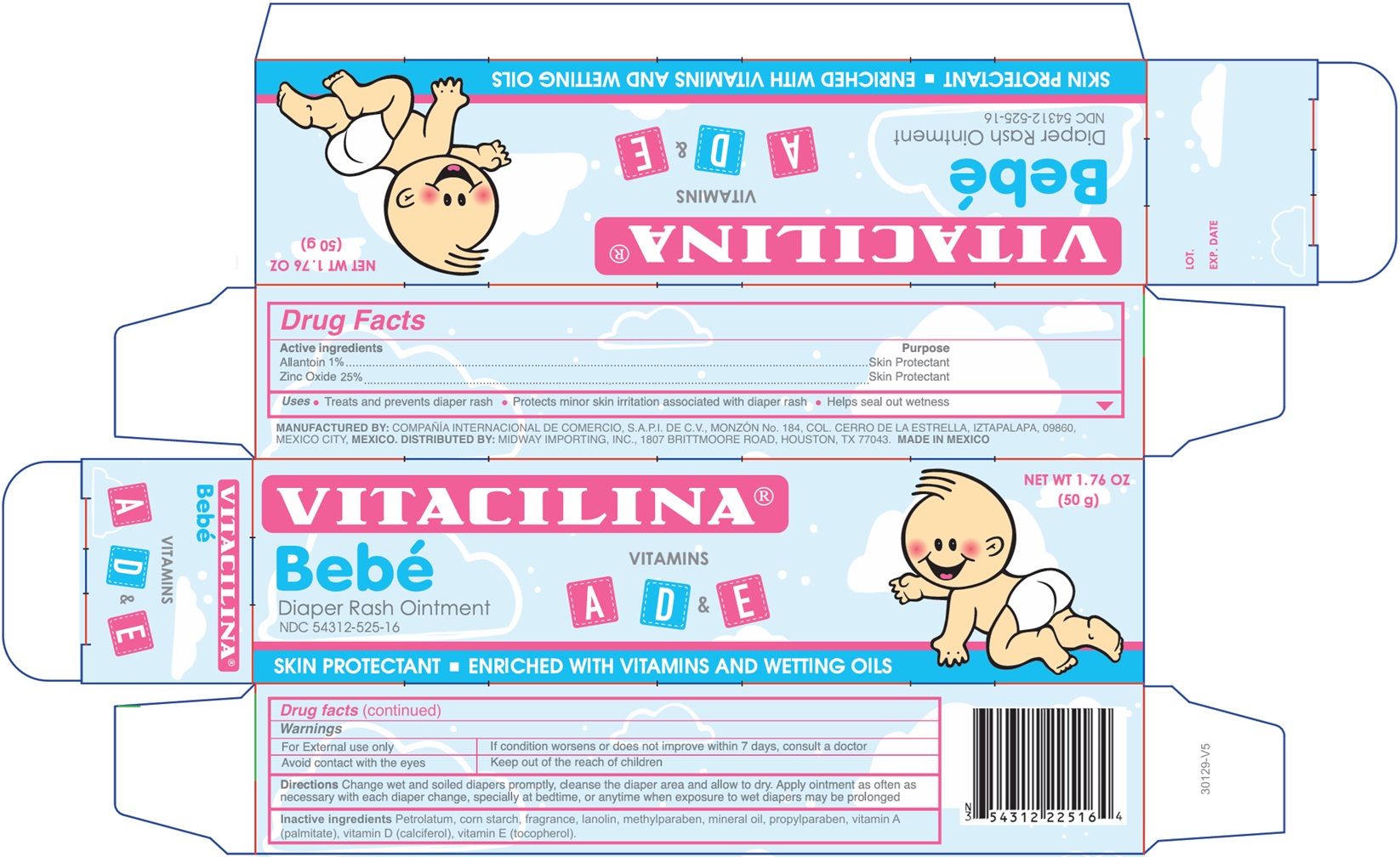 DRUG LABEL: VITACILINA Bebe Diaper Rash
NDC: 54312-525 | Form: OINTMENT
Manufacturer: Compania Internacional de Comercio, S.A.P.I de C.V.
Category: otc | Type: HUMAN OTC DRUG LABEL
Date: 20251229

ACTIVE INGREDIENTS: ALLANTOIN 10 mg/1 g; ZINC OXIDE 250 mg/1 g
INACTIVE INGREDIENTS: PETROLATUM; STARCH, CORN; LANOLIN; METHYLPARABEN; MINERAL OIL; PROPYLPARABEN; VITAMIN A; VITAMIN D; .ALPHA.-TOCOPHEROL

VITACILINA Bebe Diaper Rash Ointment

Active ingredients

Allantoin 1%

Zinc Oxide 25%

Purpose

Skin Protectant

Uses

• Helps treat and prevent diaper rash • Protects against minor skin irritation associated with diaper rash • Helps seal out wetness.

Warnings

For external use only.

When using this product

- avoid contact with the eyes.

Stop use and ask a doctor if

- condition worsens
- symptoms last more than 7 days or clear up and occur again within a few days.

Directions

• Change wet and soiled diapers promptly, cleanse the diaper area and allow to dry. • Apply ointment as often as necessary with each diaper change, especially at bedtime, or anytime when exposure to wet diapers may be prolonged.

Inactive Ingredients

Petrolatum, Corn starch, Fragrance, Lanolin, Methylparaben, Mineral oil, Propylparaben, Vitamin A Palmitate, Vitamin D (calciferol), Vitamin E (tocopherol).

Questions or comments?

Call 1-855-289-3205 (toll-free) or email contact@ksklab.us